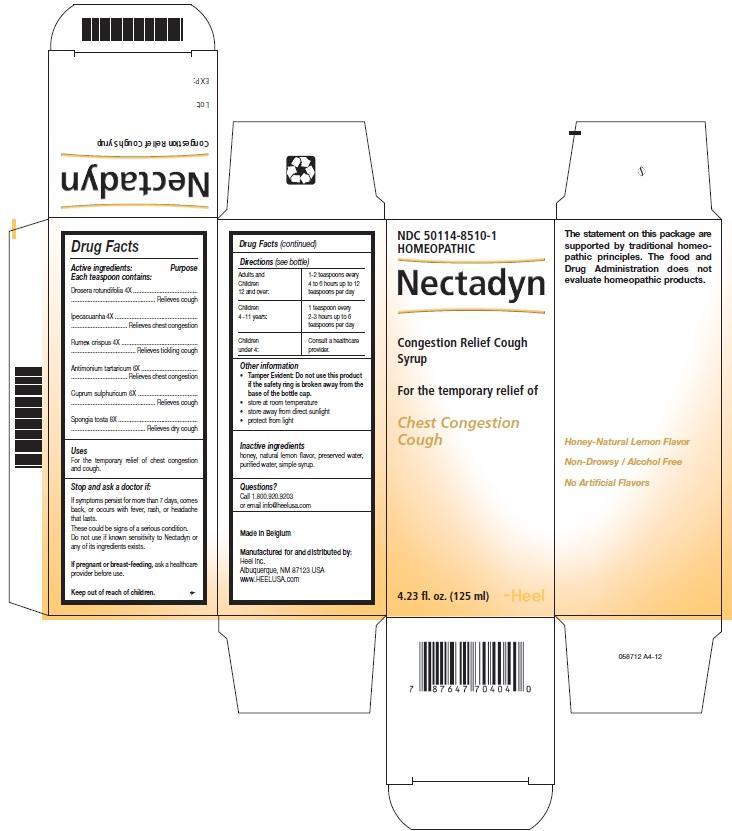 DRUG LABEL: Nectadyn
NDC: 50114-8510 | Form: SYRUP
Manufacturer: Heel Inc
Category: homeopathic | Type: HUMAN OTC DRUG LABEL
Date: 20130115

ACTIVE INGREDIENTS: DROSERA ROTUNDIFOLIA 4 [hp_X]/125 mL; IPECAC 4 [hp_X]/125 mL; RUMEX CRISPUS ROOT 4 [hp_X]/125 mL; ANTIMONY POTASSIUM TARTRATE 6 [hp_X]/125 mL; CUPRIC SULFATE 6 [hp_X]/125 mL; SPONGIA OFFICINALIS SKELETON, ROASTED 8 [hp_X]/125 mL
INACTIVE INGREDIENTS: HONEY; WATER; SUCROSE; LEMON OIL; PROPYLENE GLYCOL; METHYLPARABEN; PROPYLPARABEN

Nectadyn Cough Syrup

PURPOSE

Drosera rotundifolia 4X.....................Relieves cough

Ipecacuanha 4X................................Relieves chest congestion

Rumex crispus 4X..............................Relieves tickling cough

Antimonium tartaricum 6X..................Relieves chest congestion

Cuprum sulphuricum 6X....................Relieves cough

Spongia tosta 8X..............................Relieves dry cough

KEEP OUT OF REACH OF CHILDREN

INDICATIONS AND USAGE

For the temporary relief of :

- Chest congestion
- Cough

WARNINGS

Stop and ask a doctor if:

If symptoms persist for more than 7 days, comes back, or occurs with fever, rash or headache that lasts. These could be signs of a serious condition. Do not use if known sensitivity to Nectadyn or any of its ingredients exists.

If pregnant or breast-feeding, ask a healthcare provider before use.

DOSAGE AND ADMINISTRATION

Directions: Adults and children 12 and over
Standard Dosage:1-2 teaspoons every 4 to 6 hours up to 12 teaspoons per day
Directions: Children 4- 11 years
Standard Dosage:1 teaspoon every 2-3 hours up to 6 teaspoons per day
Directions: Children under 4 years
Standard Dosage:Consult a healthcare provider

ACTIVE INGREDIENTS

Active ingredients: Drosera rotundifolia 4X, Ipecacuanha 4X, Rumex crispus 4X, Antimonium tartaricum 6X, Cuprum sulphuricum 6X, Spongia tosta 8X.

INACTIVE INGREDIENTS

Inactive ingredients: honey, natural lemon flavor, preserved water, purified water, simple syrup